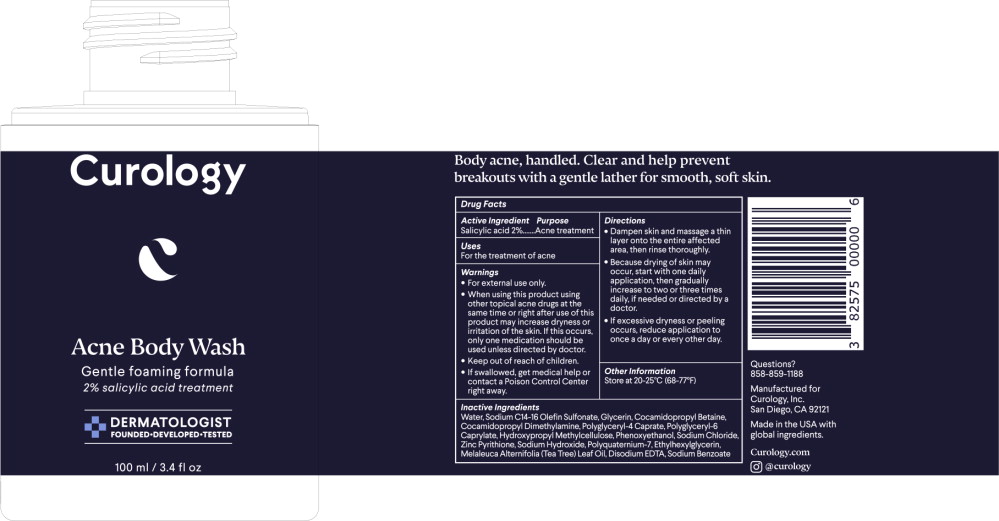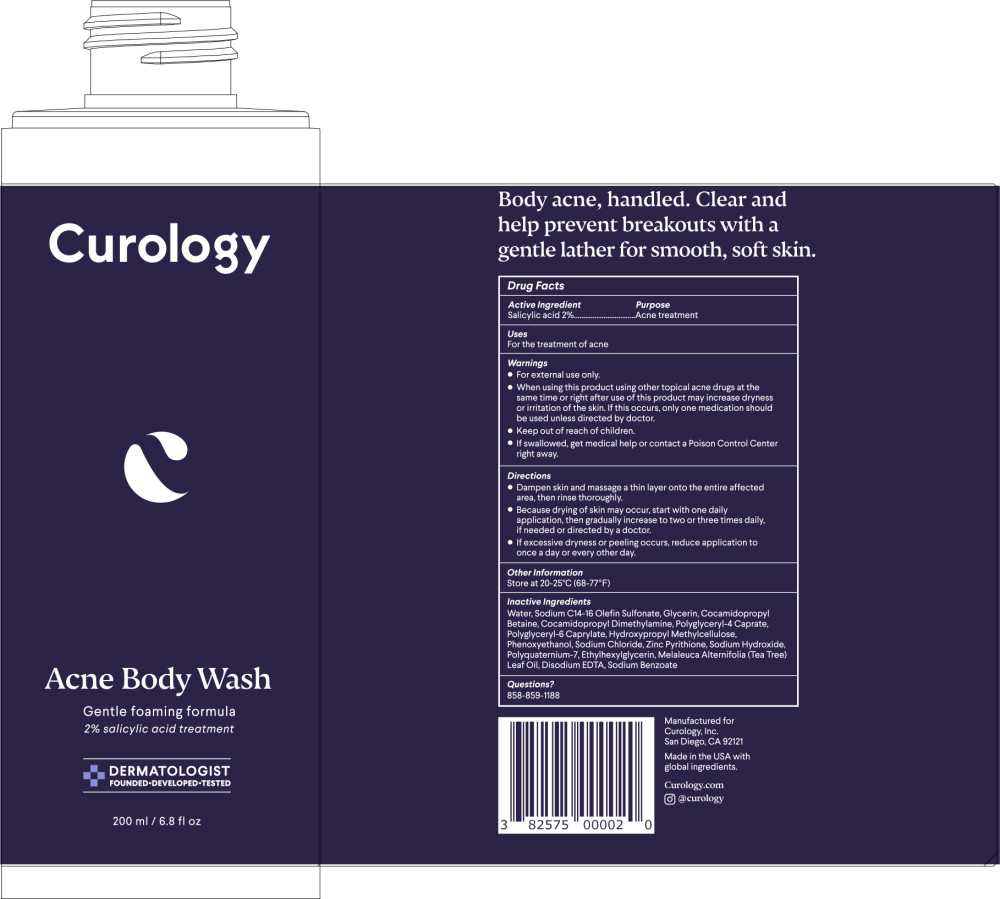 DRUG LABEL: Acne Body Wash
NDC: 82575-100 | Form: SOAP
Manufacturer: Curology
Category: otc | Type: HUMAN OTC DRUG LABEL
Date: 20251015

ACTIVE INGREDIENTS: SALICYLIC ACID 20 mg/1 mL
INACTIVE INGREDIENTS: WATER; SODIUM C14-16 OLEFIN SULFONATE; GLYCERIN; COCAMIDOPROPYL BETAINE; COCAMIDOPROPYL DIMETHYLAMINE; HYPROMELLOSE, UNSPECIFIED; POLYGLYCERYL-4 CAPRATE; POLYGLYCERYL-6 CAPRYLATE; PHENOXYETHANOL; PYRITHIONE ZINC; POLYQUATERNIUM-7 (70/30 ACRYLAMIDE/DADMAC; 1600000 MW); ETHYLHEXYLGLYCERIN; SODIUM HYDROXIDE; EDETATE DISODIUM ANHYDROUS; TEA TREE OIL; SODIUM CHLORIDE; EDETIC ACID; SODIUM BENZOATE; FORMALDEHYDE/SODIUM NAPHTHALENESULFONATE COPOLYMER (3000 MW); XANTHAN GUM; MAGNESIUM NITRATE; METHYLCHLOROISOTHIAZOLINONE; MAGNESIUM CHLORIDE; METHYLISOTHIAZOLINONE

Acne Body Wash (82575-110)

Active Ingredient

Salicylic acid 2%

Purpose

Acne treatment

Uses

For the treatment of acne

Warnings

- For external use only.

- When using this product using other topical acne drugs at the same time or right after use of this product may increase dryness or irritation of the skin. If this occurs, only one medication should be used unless directed by doctor.

- Keep out of reach of children.
- If swallowed, get medical help or contact a Poison Control Center right away.

Directions

- Dampen skin and massage a thin layer onto the entire affected area, then rinse thoroughly.
- Because drying of skin may occur, start with one daily application, then gradually increase to two or three times daily, if needed or directed by a doctor.
- If excessive dryness or peeling occurs, reduce application to once a day or every other day.

Other Information

Store at 20-25°C (68-77°F)

Inactive Ingredients

Water, Sodium C14-16 Olefin Sulfonate, Glycerin, Cocamidopropyl Betaine, Cocamidopropyl Dimethylamine, Polyglyceryl-4 Caprate, Polyglyceryl-6 Caprylate, Hydroxypropyl Methylcellulose, Phenoxyethanol, Sodium Chloride, Zinc Pyrithione, Sodium Hydroxide, Polyquaternium-7, Ethylhexylglycerin, Melaleuca Alternifolia (Tea Tree) Leaf Oil, Disodium EDTA, Sodium Benzoate

Principal Display Panel - 100 ml Bottle Label

Curology

Acne Body Wash

Gentle foaming formula

2% salicylic acid treatment

DERMATOLOGIST

FOUNDED DEVELOPED TESTED

100 ml/3.4 fl oz

Principal Display Panel - 200 ml Bottle Label

Curology

Acne Body Wash

Gentle foaming formula

2% salicylic acid treatment

DERMATOLOGIST

FOUNDED DEVELOPED TESTED

200 ml/6.8 fl oz